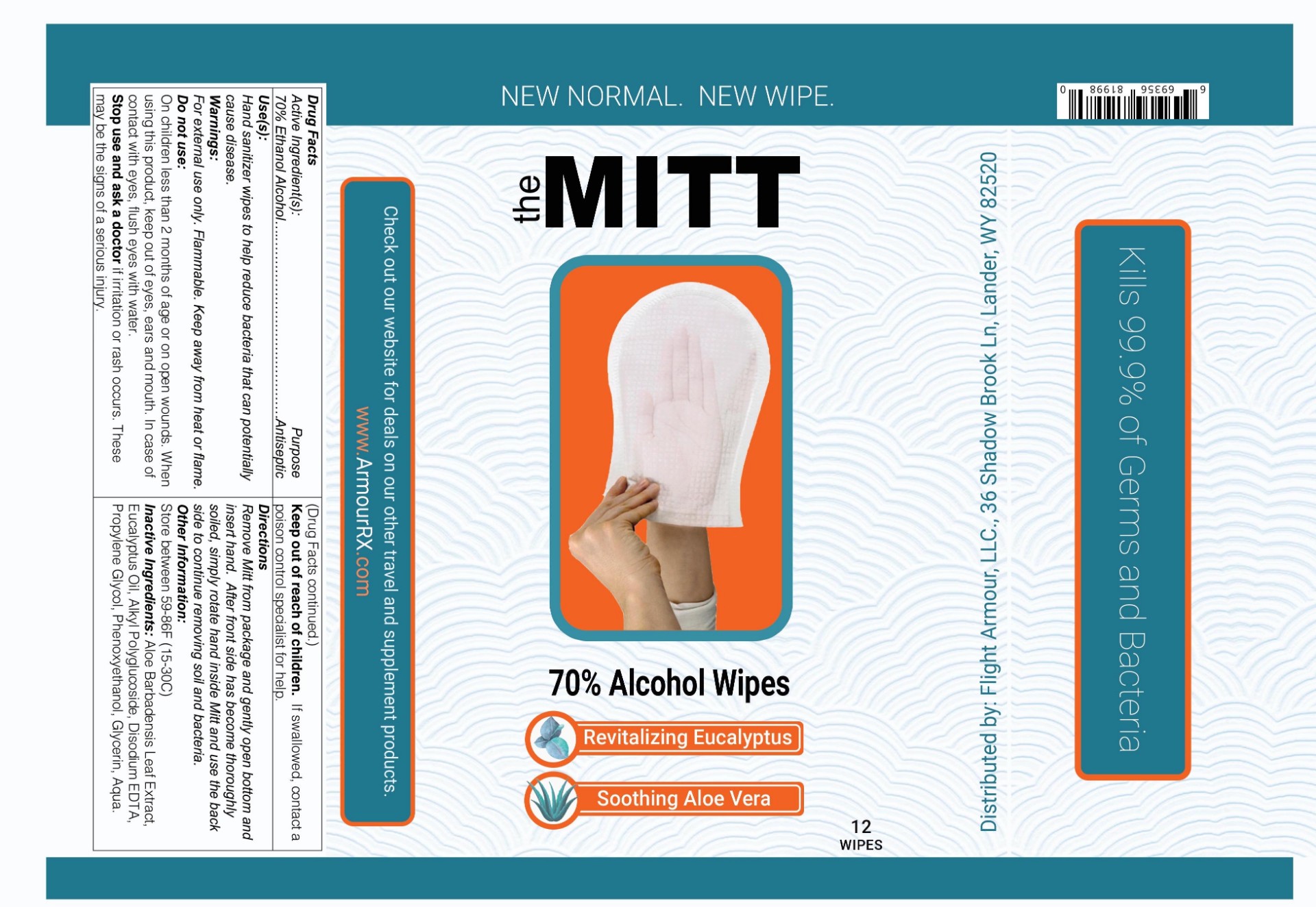 DRUG LABEL: The Mitt
NDC: 80122-111 | Form: CLOTH
Manufacturer: Flight Armour LLC
Category: otc | Type: HUMAN OTC DRUG LABEL
Date: 20200822

ACTIVE INGREDIENTS: ALCOHOL 70 mL/100 mL
INACTIVE INGREDIENTS: LAURYL GLUCOSIDE; EDETATE DISODIUM ANHYDROUS; PHENOXYETHANOL; GLYCERIN; ALOE VERA LEAF; WATER; EUCALYPTUS OIL; PROPYLENE GLYCOL

Flight Armour- The MITT Hand Wipes

Active Ingredient(s)

Alcohol 70% v/v. Purpose: Antiseptic

Purpose

Antiseptic, Hand Sanitizer

Use

Hand Sanitizer wipes to help reduce bacteria that potentially can cause disease.

Warnings

For external use only. Flammable. Keep away from heat or flame

Do not use

- in children less than 2 months of age
- on open skin wounds

When using this product keep out of eyes, ears, and mouth. In case of contact with eyes, rinse eyes thoroughly with water.
Stop use and ask a doctor if irritation or rash occurs. These may be signs of a serious condition.
Keep out of reach of children. If swallowed, get medical help or contact a Poison Control Center right away.

Stop use and ask a doctor if irritation or rash occurs. These may be signs of a serious condition.

Keep out of reach of children. If swallowed, get medical help or contact a Poison Control Center right away.

Directions

Remove Mitt from the package and gently open bottom and insert hand. After the bottom has become thoroughly soiled, simply rotate hand inside Mitt and use the backside to continue removing soil and bacteria.

Other information

- Store between 15-30C (59-86F)

Inactive ingredients

Aloe Barbadensis Leaf, Eucalyptus oil, Alkyl polyglucoside, Disodium EDTA, Propylene glycol, Glycerin, Phenoxyethanol, Aqua